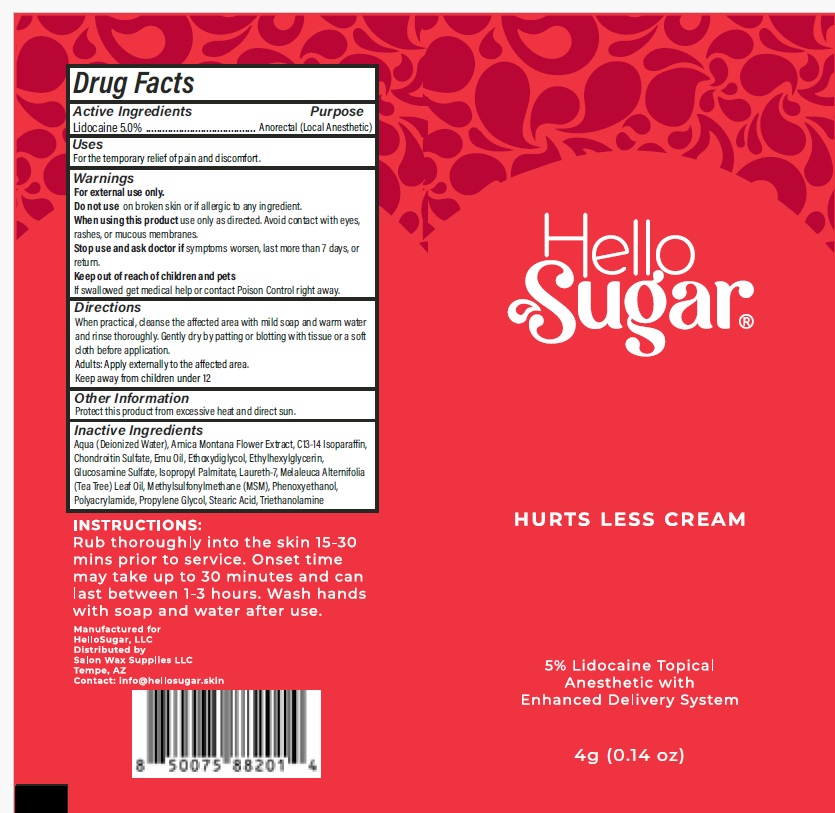 DRUG LABEL: Hello Sugar
NDC: 54723-031 | Form: CREAM
Manufacturer: Sambria Pharmaceuticals, LLC
Category: otc | Type: HUMAN OTC DRUG LABEL
Date: 20251112

ACTIVE INGREDIENTS: LIDOCAINE HYDROCHLORIDE 5 g/100 g
INACTIVE INGREDIENTS: ARNICA MONTANA FLOWER; C13-14 ISOPARAFFIN; DIMETHYL SULFONE; EMU OIL; DIETHYLENE GLYCOL MONOETHYL ETHER; ETHYLHEXYLGLYCERIN; GLUCOSAMINE SULFATE; ISOPROPYL PALMITATE; LAURETH-7; TEA TREE OIL; PHENOXYETHANOL; POLYACRYLAMIDE (10000 MW); PROPYLENE GLYCOL; CHONDROITIN SULFATE (PORCINE; 5500 MW); STEARIC ACID; TROLAMINE; WATER

Active ingredient

Lidocaine HCL 5.0% w/w

Purpose

Anorectal (Local Anesthetic)

Uses

For temporary relief of pain and discomfort

Warnings

For external use only.

Do not use on broken skin or if allergic to any ingredient.

When using this product use only as directed. Avoid contact with the eyes, rashes, or mucous membranes.

Stop use and ask doctor if condition worsens, or if symptoms persist for more than 7 days or return.

Keep out of reach of children and pets If swallowed get medical help or contact a Poison Control Center right away.

Directions

When Practical, cleanse the affected area with mild soap and warm water and rinse thoroughly. Gently dry by patting or blotting with tissue or a soft cloth before application.

Adults: Apply externally to the affected area.

Keep away from children under 12

Other information

Protect this product from excessive heat and direct sun.

Inactive ingredients

Aqua (Deionized Water), Arnica Montana Flower Extract, C13-14 Isoparaffin, Chondroitin Sulfate, Emu Oil, Ethoxydiglycol, Ethylhexylglycerin, Glucosamine Sulfate, Isopropyl Palmitate, Laureth-7, Melaleuca Alternifolia (Tea Tree) Leaf Oil, Methylsulfonylmethane (MSM), Phenoxyethanol, Polyacrylamide, Propylene Glycol, Stearic Acid, Triethanolamine